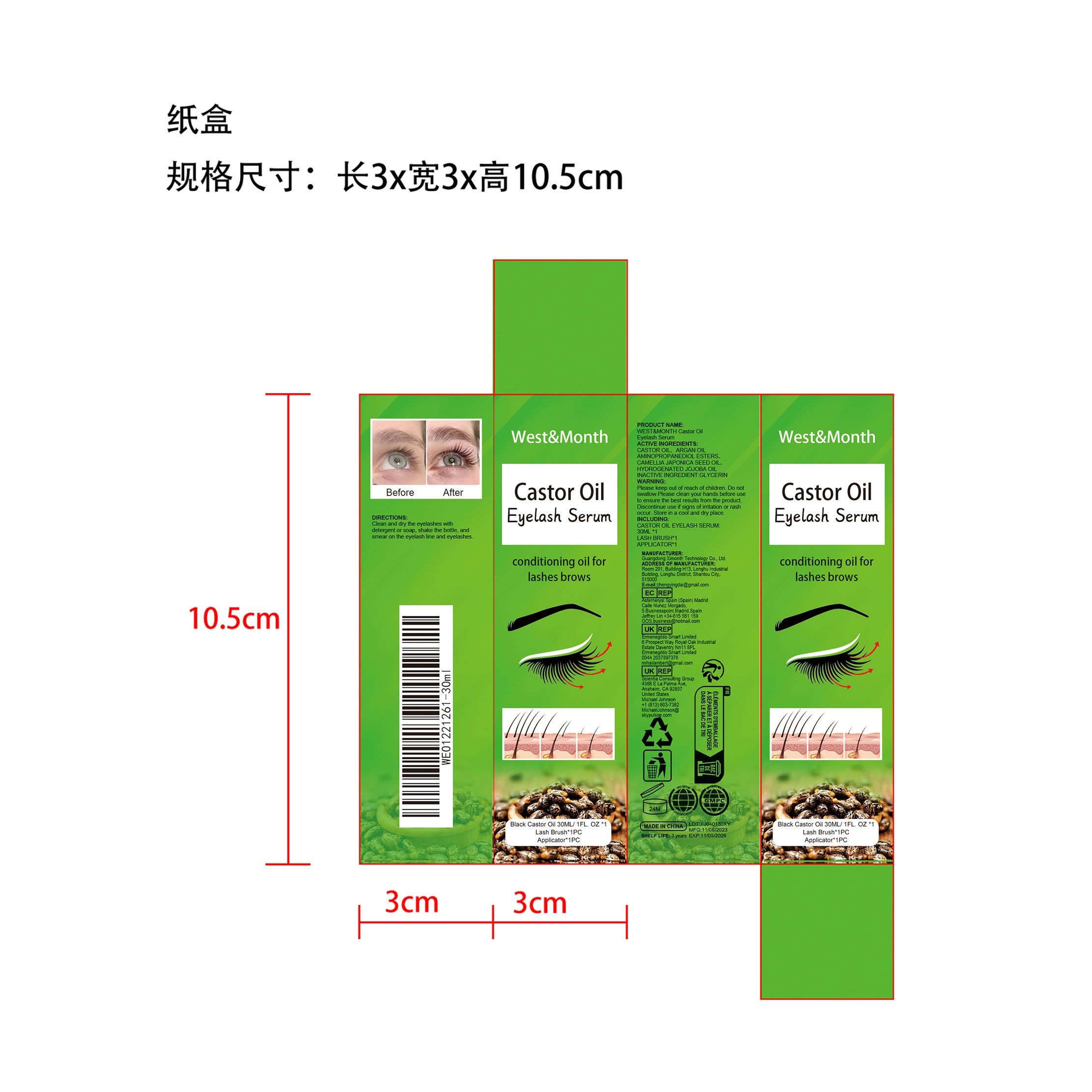 DRUG LABEL: WEST MONTH Castor Oil Eyelash Serum
NDC: 84660-050 | Form: OIL
Manufacturer: Guangdong Ximonth Technology Co., Ltd.
Category: otc | Type: HUMAN OTC DRUG LABEL
Date: 20241028

ACTIVE INGREDIENTS: CASTOR OIL 3 mg/30 mg; ARGAN OIL AMINOPROPANEDIOL ESTERS 9 mg/30 mg; CAMELLIA JAPONICA SEED OIL 7.5 mg/30 mg; HYDROGENATED JOJOBA OIL 4.5 mg/30 mg
INACTIVE INGREDIENTS: GLYCERIN 6 mg/30 mg

Active Ingredient(s)

CASTOR OIL、ARGAN OIL AMINOPROPANEDIOL ESTERS、CAMELLIA JAPONICA SEED OIL、 HYDROGENATED JOJOBA OIL

Purpose

Conditioning oil for lashes brows

Use

Clean and dry the eyelashes withdetergent or soap, shake the bottle, and smear on the eyelash line and eyelashes.

Warnings

Please keep out of reach of children.Do not swallow.Please clean your hands before use to ensure the best results from the product.Discontinue use if signs of irritation or rash occur.Store in a cool and dry place.

Do not use

Discontinue use if signs of irritation or rash occur.

Stop Use

Discontinue use if signs of irritation or rash occur.

STORAGE AND HANDLING

Please keep out of reach of children. Do not swallow.

KEEP OUT OF REACH OF CHILDREN

Please keep out of reach of children. Do not swallow.

INACTIVE INGREDIENT

GLYCERIN